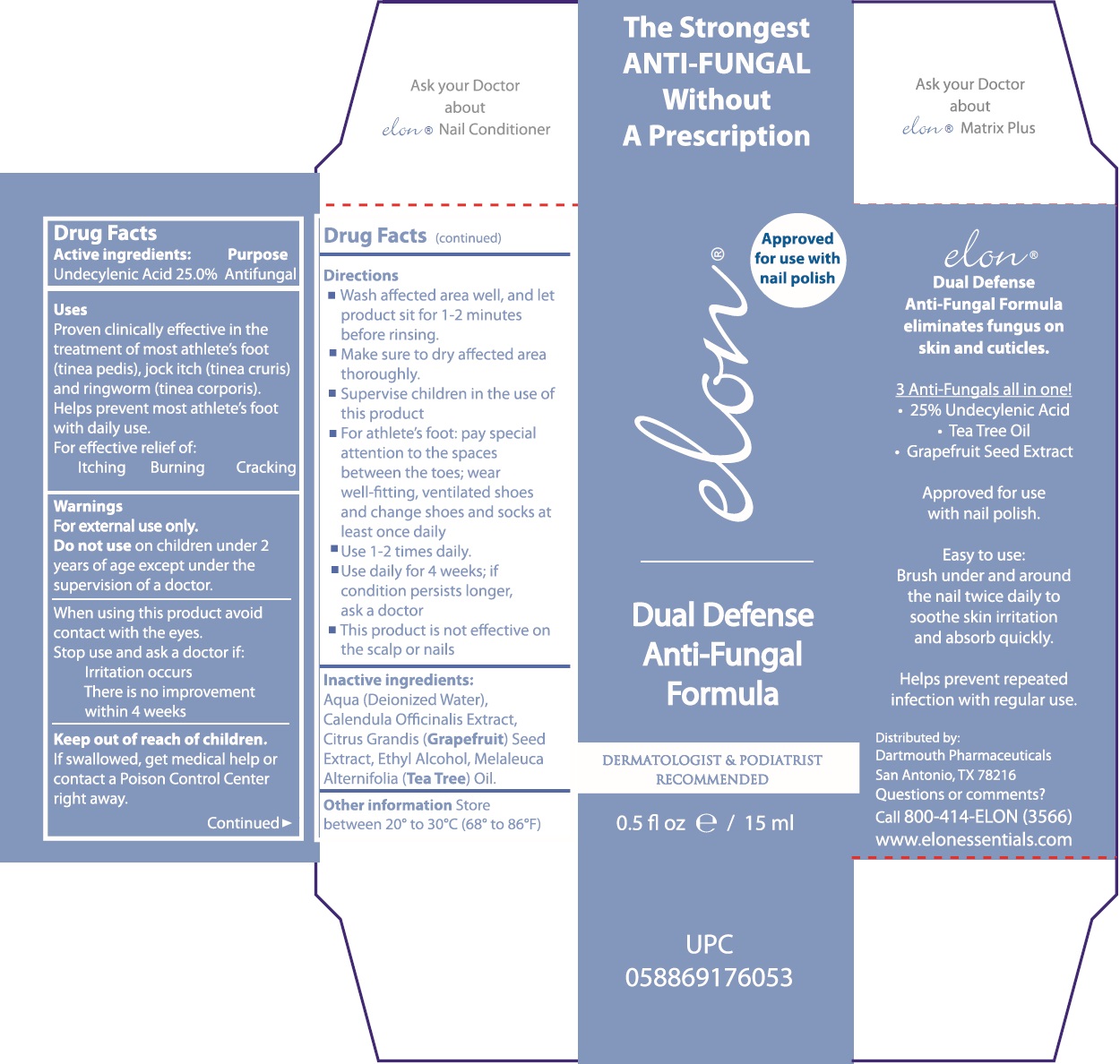 DRUG LABEL: ELON Dual Defense Anti Fungal Formula
NDC: 71171-778 | Form: LIQUID
Manufacturer: Little Giant Holdings LLC
Category: otc | Type: HUMAN OTC DRUG LABEL
Date: 20250128

ACTIVE INGREDIENTS: UNDECYLENIC ACID 250 mg/1 mL
INACTIVE INGREDIENTS: WATER; CALENDULA OFFICINALIS FLOWER	; CITRUS MAXIMA SEED; ALCOHOL; TEA TREE OIL

ELON Dual Defense Anti-Fungal Formula

Active ingredients:

Undecylenic Acid 25.0%

Purpose

Antifungal

Uses

Proven clinically effective in the treatment of most athletes's foot (tinea pedis), jock itch (tinea cruris) and ringworm (tinea corporis). Helps prevent most athlete's foot with daily use.

For effective relief of:

Itching Burning Cracking

Warnings

For external use only.

Do not use

on children under 2 years of age except under the supervision of a doctor.

When using this product

avoid contact with the eyes.

Stop use and ask a doctor if:

Irritation occurs There is no improvement within 4 weeks

Keep out of reach of children.

If swallowed, get medical help or contact a Poison Control Center right away.

Directions

- Wash affected area well, and let product sit for 1-2 minutes before rinsing.
- Make sure to dry affected area thoroughly.
- Supervise children in the use of this product
- For athlete's foot: pay special attention to the spaces between the toes; wear well-fitting, ventilated shoes and change shoes and socks at leat once daily
- Use 1-2 times daily.
- Use daily for 4 weeks; if condition persists longer, ask a doctor
- This product is not effective on the scalp or nails

Inactive ingredients:

Aqua (Deionized Water), Calendula Officianalis Extract, Citrus Grandis (Grapefruit) Seed Extract, Ethyl Alcohol, Melaleuca Alternifolia (Tea Tree) Oil.

Other information

Store between 20° to 30°C (68° to 86°F)